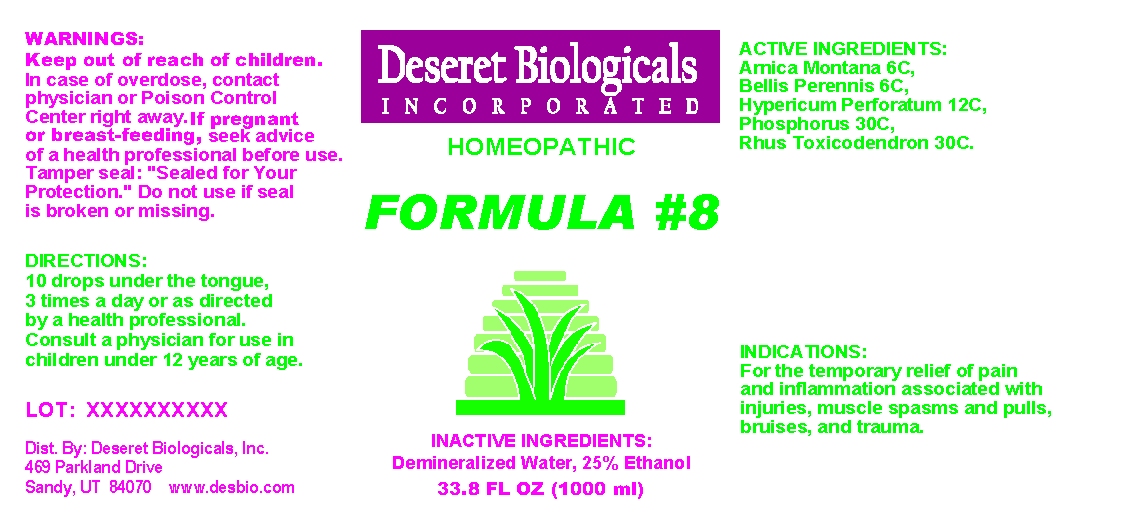 DRUG LABEL: Formula 8
NDC: 57520-0201 | Form: LIQUID
Manufacturer: Apotheca Company
Category: homeopathic | Type: HUMAN OTC DRUG LABEL
Date: 20100625

ACTIVE INGREDIENTS: ARNICA MONTANA 6 [hp_C]/1 mL; BELLIS PERENNIS 6 [hp_C]/1 mL; HYPERICUM PERFORATUM 12 [hp_C]/1 mL; PHOSPHORUS 30 [hp_C]/1 mL; TOXICODENDRON PUBESCENS LEAF 30 [hp_C]/1 mL
INACTIVE INGREDIENTS: WATER; ALCOHOL

Formula 8

ACTIVE INGREDIENT

ACTIVE INGREDIENTS: Arnica Montana 6C, Bellis Perennis 6C, Hypericum Perforatum 12C, Phosphorus 30C, Rhus Toxicodendron.

PURPOSE

INDICATIONS: For the temporary relief of pain and inflammation associated with injuries, muscle spasms and pulls, bruises, and trauma.

WARNINGS

WARNINGS: Keep out of reach of children. In case of overdose, contact physician or Poison Control Center right away.

If pregnant or breast-feeding, seek advice of a health professional before use.

Tamper seal: "Sealed for your protection." Do not use if seal is broken or missing.

DOSAGE AND ADMINISTRATION

DIRECTIONS: 10 drops under the tongue, 3 times a day or as directed by a health professional. Consult a physician for use in children under 12 years of age.

INACTIVE INGREDIENTS: Demineralized Water, 25% Ethanol

QUESTIONS

Dist. By:

Deseret Biologicals, Inc.

469 Parkland Drive

Sandy, UT 84070

www.desbio.com

PACKAGE LABEL

Deseret Biologicals Incorporated

HOMEOPATHIC

FORMULA #8

33.8 FL OZ (1000 ML)